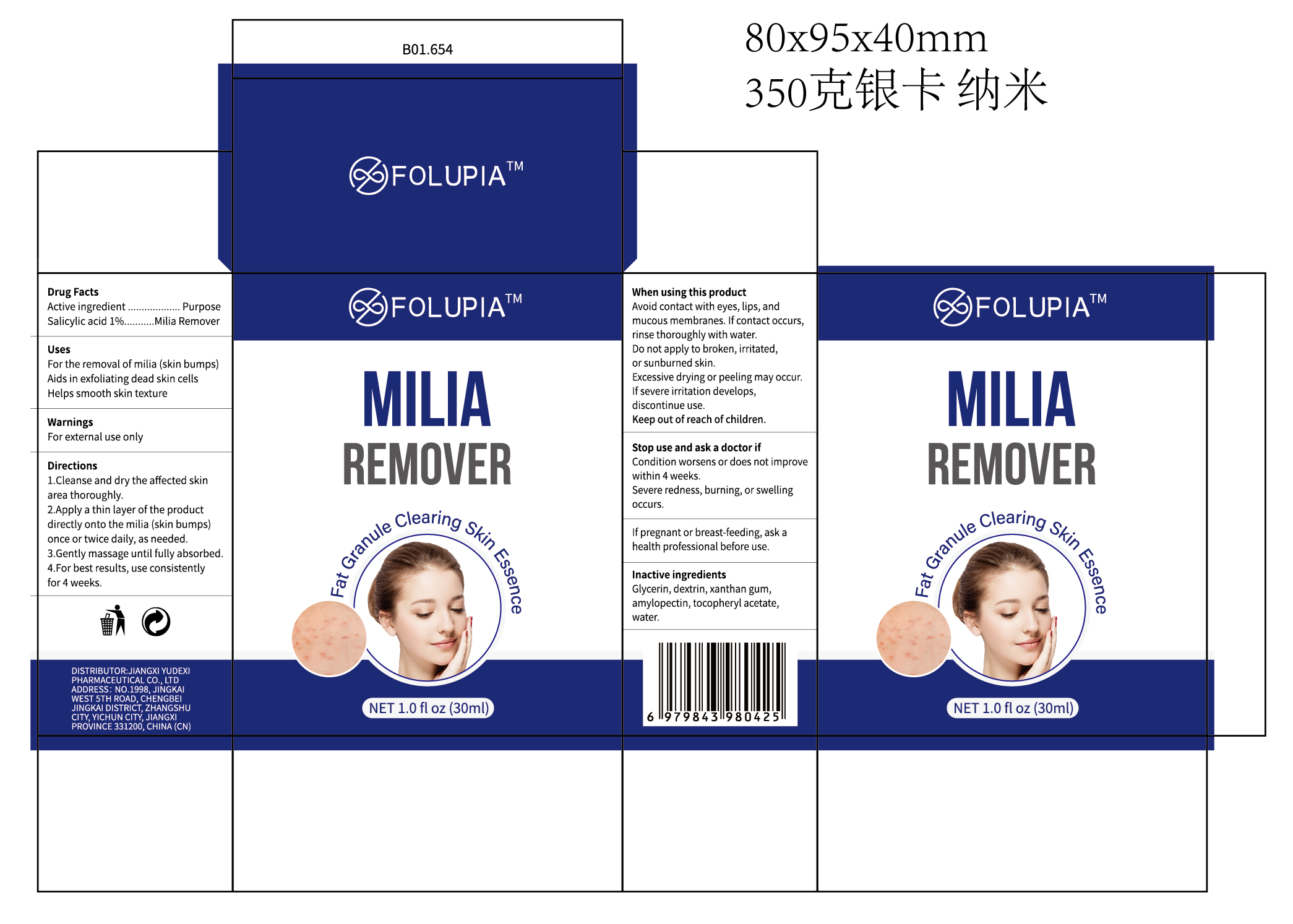 DRUG LABEL: FOLUPIA  MILIA REMOVER
NDC: 85248-147 | Form: LIQUID
Manufacturer: Jiangxi Yudexi Pharmaceutical Co., LTD
Category: otc | Type: HUMAN OTC DRUG LABEL
Date: 20260227

ACTIVE INGREDIENTS: SALICYLIC ACID 1 g/100 mL
INACTIVE INGREDIENTS: DEXTRIN, CORN; GLYCERIN; XANTHAN GUM; .ALPHA.-TOCOPHEROL ACETATE; AMYLOPECTIN, CORN; WATER

85248-147

Active Ingredient

Salicylic acid 1%

Purpose

Milia Remover

Use

For the removal of milia (skin bumps)Aids in exfoliating dead skin cells Helps smooth skin texture

Warnings

For external use only,

Do not use

condition worsens or does not improve within 4 weeks,Severe redness, burning, or swelling occurs.
If pregnant or breast-feeding, ask a health professional before use.

When Using

Avoid contact with eyes.lips.and mucous membranes. If contact occurs,rinse thoroughly with water. Do not apply to broken,irritated,or sunburned skin.Excessive drying or peeling may occur.If severe irritation develops,discontinue use.

Stop Use

condition worsens or does not improve within 4 weeks,Severe redness, burning, or swelling occurs.
If pregnant or breast-feeding, ask a health professional before use.

Ask Doctor

condition worsens or does not improve within 4 weeks,Severe redness, burning, or swelling occurs.
If pregnant or breast-feeding, ask a health professional before use.

Keep Oot Of Reach Of Children

Keep out of reach of children.

Directions

1.Cleanse and dry the affected skin area thoroughly.2.Apply a thin layer of the product directly onto the milia (skin bumps） once or twice daily, as needed.3.Gently massage until fully absorbed.4.For best results, use consistently for 4 weeks.

Inactive ingredients

Glycerin, dextrin,xanthan gum,amylopectin, tocopheryl acetate.water.